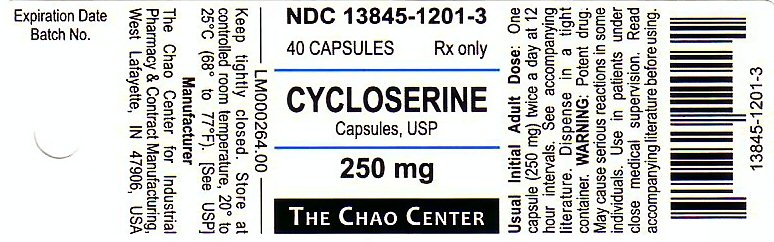 DRUG LABEL: CYCLOSERINE
NDC: 13845-1201 | Form: CAPSULE
Manufacturer: Parsolex Gmp Center, Inc.
Category: prescription | Type: HUMAN PRESCRIPTION DRUG LABEL
Date: 20230119

ACTIVE INGREDIENTS: CYCLOSERINE 250 mg/250 mg
INACTIVE INGREDIENTS: TITANIUM DIOXIDE; FERROSOFERRIC OXIDE; FD&C BLUE NO. 1; FD&C RED NO. 3; FD&C YELLOW NO. 6; D&C YELLOW NO. 10; SODIUM LAURYL SULFATE; GELATIN; BENZYL ALCOHOL; SODIUM PROPIONATE; PROPYLPARABEN; BUTYLPARABEN; METHYLPARABEN

DESCRIPTION SECTION

Cycloserine, 3-isoxazolidinone, 4-amino –, (R)– is a broad–spectrum antibiotic that is produced by a strain of Streptomyces orchidaceus and has also been synthesized. Cycloserine is a white to off–white powder that is soluble in water and stable in alkaline solution. It is rapidly destroyed at a neutral or acid pH.
Cycloserine has a pH between 5.5 and 6.5 in a solution containing 100 mg/mL. The molecular weight of cycloserine is 102.09, and it has an empirical formula of C3H6N2O2.

INACTIVE INGREDIENT SECTION

Each capsule contains cycloserine, 250 mg (2.45 mmol); D and C Yellow No. 10, FD and C Blue No. 1, FD and C Red No. 3, FD and C Yellow No. 6, gelatin, iron oxide, talc, titanium dioxide, and other inactive ingredients.

CLINICAL PHARMACOLOGY SECTION

After oral administration, cycloserine is readily absorbed from the gastrointestinal tract, with peak blood levels occurring in 4 to 8 hours.
Blood levels of 25 to 30 μg/mL can generally be maintained with the usual dosage of 250 mg twice a day, although the relationship of plasma levels to dosage is not always consistent. Concentrations in the cerebrospinal fluid, pleural fluid, fetal blood, and mother’s milk approach those found in the serum. Detectable amounts are found in ascitic fluid, bile, sputum, amniotic fluid, and lung and lymph tissues. Approximately 65 percent of a single dose of cycloserine can be recovered in the urine within 72 hours after oral administration. The remaining 35 percent is apparently metabolized to unknown substances. The maximum excretion rate occurs 2 to 6 hours after administration, with 50 percent of the drug eliminated in 12 hours.

MICROBIOLOGY SECTION

Cycloserine inhibits cell–wall synthesis in susceptible strains of gram–positive and gram–negative bacteria and in Mycobacterium tuberculosis.

Susceptibility Tests
Cycloserine clinical laboratory standard powder is available for both direct and indirect methods1 of determining the susceptibility
of strains of mycobacteria. Cycloserine MICs for susceptible strains are 25 μg/mL or lower.

INDICATIONS & USAGE SECTION

Cycloserine is indicated in the treatment of active pulmonary and extrapulmonary tuberculosis (including renal disease) when the causative
organisms are susceptible to this drug and when treatment with the primary medications (streptomycin, isoniazid, rifampin, and ethambutol) has proved inadequate. Like all antituberculosis drugs, cycloserine should be administered in conjunction with other effective chemotherapy and not as the sole therapeutic agent.
Cycloserine may be effective in the treatment of acute urinary tract infections caused by susceptible strains of gram–positive and gram–negative bacteria, especially Enterobacter spp. and Escherichia coli. It is generally no more and is usually less effective than other antimicrobial agents in the treatment of urinary tract infections caused by bacteria other than mycobacteria. Use of cycloserine in these infections should be considered only when more conventional therapy has failed and when the organism has been demonstrated to be susceptible to the drug.

CONTRAINDICATIONS SECTION

Administration is contraindicated in patients with any of the
following:
Hypersensitivity to cycloserine
Epilepsy
Depression, severe anxiety, or psychosis
Severe renal insufficiency
Excessive concurrent use of alcohol

WARNINGS SECTION

Administration of cycloserine should be discontinued or the dosage reduced if the patient develops allergic dermatitis or symptoms of CNS toxicity, such as convulsions, psychosis, somnolence, depression, confusion, hyperreflexia, headache, tremor, vertigo, paresis, or dysarthria.
The toxicity of cycloserine is closely related to excessive blood levels (above 30 μg/mL), as determined by high dosage or inadequate renal clearance. The ratio of toxic dose to effective dose in tuberculosis is small.
The risk of convulsions is increased in chronic alcoholics.
Patients should be monitored by hematologic, renal excretion, blood level, and liver function studies.

PRECAUTIONS SECTION

Before treatment with cycloserine is initiated, cultures should be taken and the organism’s susceptibility to the drug should be established. In
tuberculous infections, the organism’s susceptibility to the other antituberculosis agents in the regimen should also be demonstrated.
Anticonvulsant drugs or sedatives may be effective in controlling symptoms of CNS toxicity, such as convulsions, anxiety, and tremor. Patients receiving more than 500 mg of cycloserine daily should be closely observed for such symptoms. The value of pyridoxine in preventing CNS toxicity from cycloserine has not been proved.
Administration of cycloserine and other antituberculosis drugs has been associated in a few instances with vitamin B12 and/or
folic–acid deficiency, megaloblastic anemia, and sideroblastic anemia. If evidence of anemia develops during treatment, appropriate studies and therapy should be instituted.

LABORATORY TESTS SECTION

Blood levels should be determined at least weekly for patients with reduced renal function, for individuals receiving a daily dosage of more
than 500 mg, and for those showing signs and symptoms suggestive of toxicity. The dosage should be adjusted to keep the blood level below 30 μg/mL.

DRUG INTERACTIONS SECTION

Concurrent administration of ethionamide has been reported to potentiate neurotoxic side effects.
Alcohol and cycloserine are incompatible, especially during a regimen calling for large doses of the latter. Alcohol increases the possibility and risk of epileptic episodes.
Concurrent administration of isoniazid may result in increased incidence of CNS effects, such as dizziness or drowsiness. Dosage adjustments may be necessary and patients should be monitored closely for signs of CNS toxicity.
Carcinogenesis, Mutagenicity, and Impairment of Fertility
Studies have not been performed to determine potential for carcinogenicity. The Ames test and unscheduled DNA repair test were negative. A study in 2 generations of rats showed no impairment of fertility relative to controls for the first mating but somewhat lower fertility in the second mating.

PREGNANCY SECTION

Pregnancy Category C
A study in 2 generations of rats given doses up to 100 mg/kg/day demonstrated no teratogenic effect in offspring. It is not known whether cycloserine can cause fetal harm when administered to a pregnant woman or can affect reproduction capacity. Cycloserine should be given to a pregnant woman only if clearly needed.

NURSING MOTHERS SECTION

Because of the potential for serious adverse reactions in nursing infants from cycloserine, a decision should be made whether to discontinue nursing or to discontinue the drug, taking into account the importance of the drug to the mother.

PEDIATRIC USE SECTION

Safety and effectiveness in pediatric patients have not been established.

ADVERSE REACTIONS SECTION

Most adverse reactions occurring during therapy with cycloserine involve the nervous system or are manifestations of drug hypersensitivity. The following side effects have been observed in patients receiving cycloserine:
Nervous system symptoms (which appear to be related to higher dosages of the drug, i.e., more than 500 mg daily)
Convulsions
Drowsiness and somnolence
Headache
Tremor
Dysarthria
Vertigo
Confusion and disorientation with loss of memory
Psychoses, possibly with suicidal tendencies
Character changes
Hyperirritability
Aggression
Paresis
Hyperreflexia
Paresthesia
Major and minor (localized) clonic seizures
Coma
Cardiovascular

Sudden development of congestive heart failure in patients receiving 1 to 1.5 g of cycloserine daily has been reported
Allergy (apparently not related to dosage)
Skin rash
Miscellaneous
Elevated serum transaminase, especially in patients with preexisting liver disease

OVERDOSAGE SECTION

Acute toxicity from cycloserine can occur if more than 1 g is ingested by an adult. Chronic toxicity from cycloserine is dose related and can occur if more than 500 mg is administered daily. Patients with renal impairment will accumulate cycloserine and may develop toxicity if the dosing regimen is not modified. Patients with severe renal impairment should not receive the drug. The central nervous system is the most common organ system involved with toxicity. Toxic effects may include headache, vertigo, confusion, drowsiness,
hyperirritability, paresthesias, dysarthria, and psychosis. Following larger ingestions, paresis, convulsions, and coma often occur. Ethyl alcohol may increase the risk of seizures in patients receiving cycloserine.
The oral median lethal dose in mice is 5290 mg/kg.
Treatment
To obtain up–to–date information about the treatment of overdose, a good resource is your certified Regional Poison Control Center. Telephone numbers of certified poison control centers are listed in the Physicians’ Desk Reference (PDR). In managing overdosage,
consider the possibility of multiple drug overdoses, interaction among drugs, and unusual drug kinetics in your patient.
Overdoses of cycloserine have been reported rarely. The following is provided to serve as a guide should such an overdose be ecountered.
Protect the patient’s airway and support ventilation and perfusion. Meticulously monitor and maintain, within acceptable limits, the patient’s vital signs, blood gases, serum electrolytes, etc. Absorption of drugs from the gastrointestinal tract may be decreased by giving activated charcoal, which, in many cases, is more effective than emesis or lavage; consider charcoal instead of or in addition to gastric emptying. Repeated doses of charcoal over time may hasten elimination of some drugs that have been absorbed. Safeguard the patient’s airway when employing gastric emptying or charcoal.
In adults, many of the neurotoxic effects of cycloserine can be both treated and prevented with the administration of 200 to 300 mg of pyridoxine daily.
The use of hemodialysis has been shown to remove cycloserine from the bloodstream. This procedure should be reserved for patients with
life-threatening toxicity that is unresponsive to less invasive therapy

DOSAGE & ADMINISTRATION SECTION

Cycloserine is effective orally and is currently administered only by this route. The usual dosage is 500 mg to 1 g daily in divided doses monitored by blood levels.2 The initial adult dosage most frequently given is 250 mg twice daily at 12–hour intervals for the first 2 weeks. A daily dosage of 1 g should not be exceeded.

HOW SUPPLIED SECTION

Cycloserine is available as a 250 mg capsule with an opaque red cap and opaque gray body imprinted with “CHAO” and “F04” in edible black ink on both the cap and the body.
Bottles of 40 NDC 13845-1201-3
Store at controlled room temperature, 20° to 25°C (68° to 77°F) [see USP].

REFERENCES SECTION

1. Kubica GP, Dye WE: Laboratory methods for clinical and public health - mycobacteriology, US Department of Health, Education, and Welfare, Public Health Services, 1967, pp47-55, 66-70.
2. Jones LR: Colorimetric determination of cycloserine, a new antibiotic. Anal Chem 1956; 28:39.
The Chao Center for Industrial Pharmacy and Contact Manufacturing West Lafayette, IN, 47906, USA
Literature revised 14 JANUARY 2009
LM000265.00 PRINTED IN USA

PACKAGE LABEL PRINCIPAL DISPLAY PANEL

CYCLOSERINE Capsules, USP 250mg THE CHAO CENTER NDC 13845-1201-3 40 capsules Rx only
Usual Initial Adult Dose: One capsule (250 mg) twice a day at 12 hour intervals. See accompanying literature. Dispense in a tight container.
WARNING: Potent drug. May cause serious reactions in some individuals. Use in patients under close medical supervision. Read accompanying literature before using.
13845-1201-3
LM000264.00
Keep tightly closed. Store at controlled room temperature, 20 degrees to 25 degrees C (68 degrees to 77 degrees F). [see USP]
Maunfacture The Chao center for Industrial Pharmacy and Contract Manufacturing, West Lafayette, IN 47906, USA
Expiration Date Batch No.